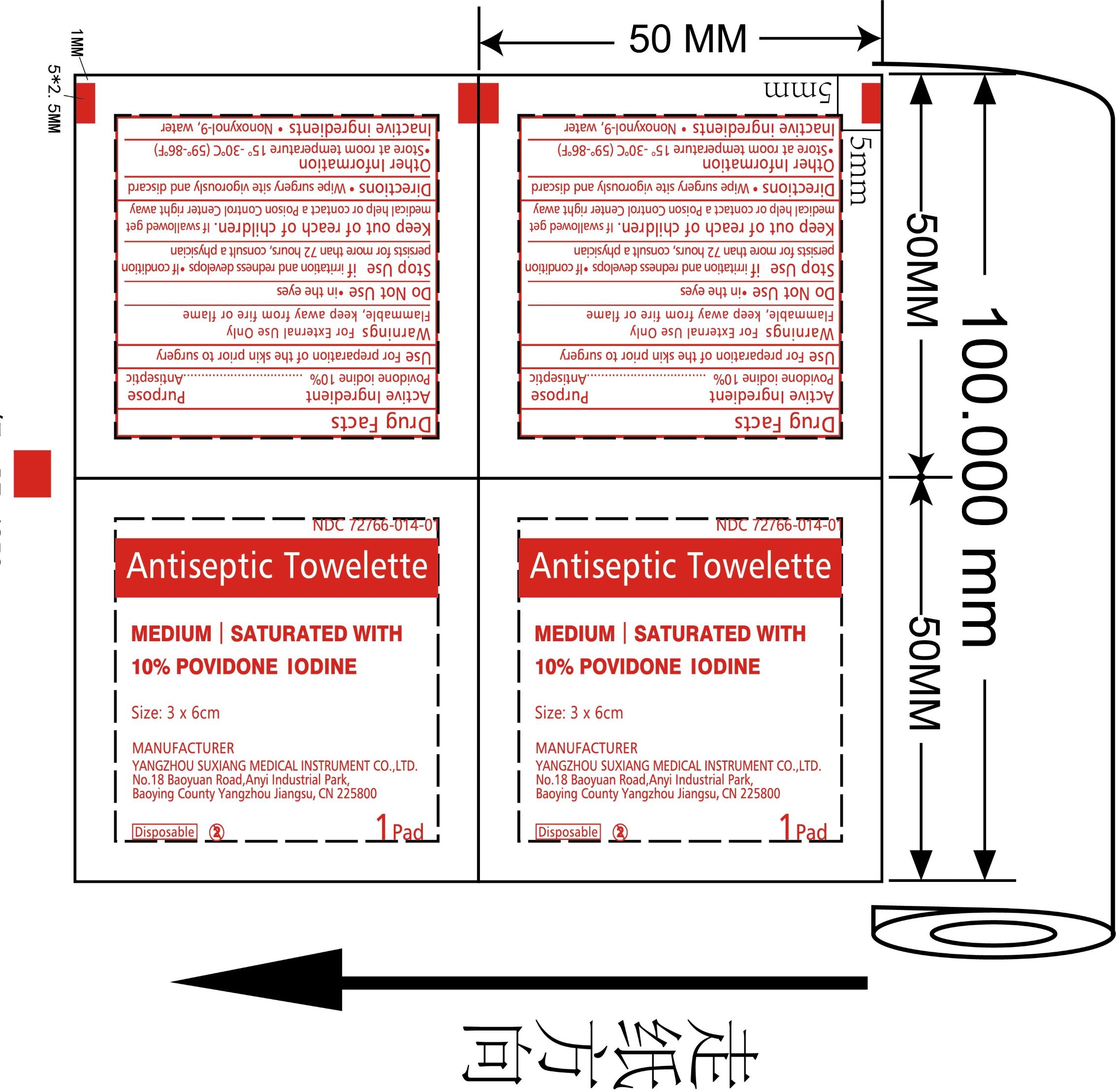 DRUG LABEL: PROVIDONE-IODINE PREP PADS
NDC: 72766-014 | Form: SWAB
Manufacturer: Yangzhou Suxiang Medical Instrument Co, LTD
Category: otc | Type: HUMAN OTC DRUG LABEL
Date: 20240305

ACTIVE INGREDIENTS: POVIDONE-IODINE 12 g/1 1
INACTIVE INGREDIENTS: WATER; NONOXYNOL-9

Providone-Iodine Prep Pads

Active Ingredient

Povidone Iodine 10%

Purpose

Antiseptic

Uses

Antiseptic cleanser to help prevent skin infection in minor cuts, scrapes, and burns

For preparation of the skin prior to surgery

Helps reduce bacteria that can potentially cause skin infection

Warnings

For External Use Only.

Do not use

In the eyes

As a first aid anticeptic for more than 1 week

Over large areas of the body

Ask a doctor before use if you have

Deep puncture wounds

Animal bites

Serious wounds

Stop use and ask a doctor if

Condition worsens or persists for more than 72 hours

Irritation and redness develops

Keep out of reach of children

If swallowed, get medical help or contact a Poison Control Center immediately

Directions

Tear a notch

Remove applicator

Use only once

As a first aid antiseptic

Clean affected area

apply 1 to 3 times daily

May be covered with sterile bandage

If bandaged, let dry first

For preoperative patient skin preparation

Clean area

Apply to operative site prior to surgery using applicator

Other Information

Store at room temperature

Avoid excessive heat

Inactive Ingredients

Nonoxynol-9, water

DOSAGE & ADMINISTRATION

Sterile unless poch is opened or damaged.

Saturated with 10% Povidone Iodine.

INDICATIONS & USAGE

For External Use Only. Apply topically as needed. Discard after single use.